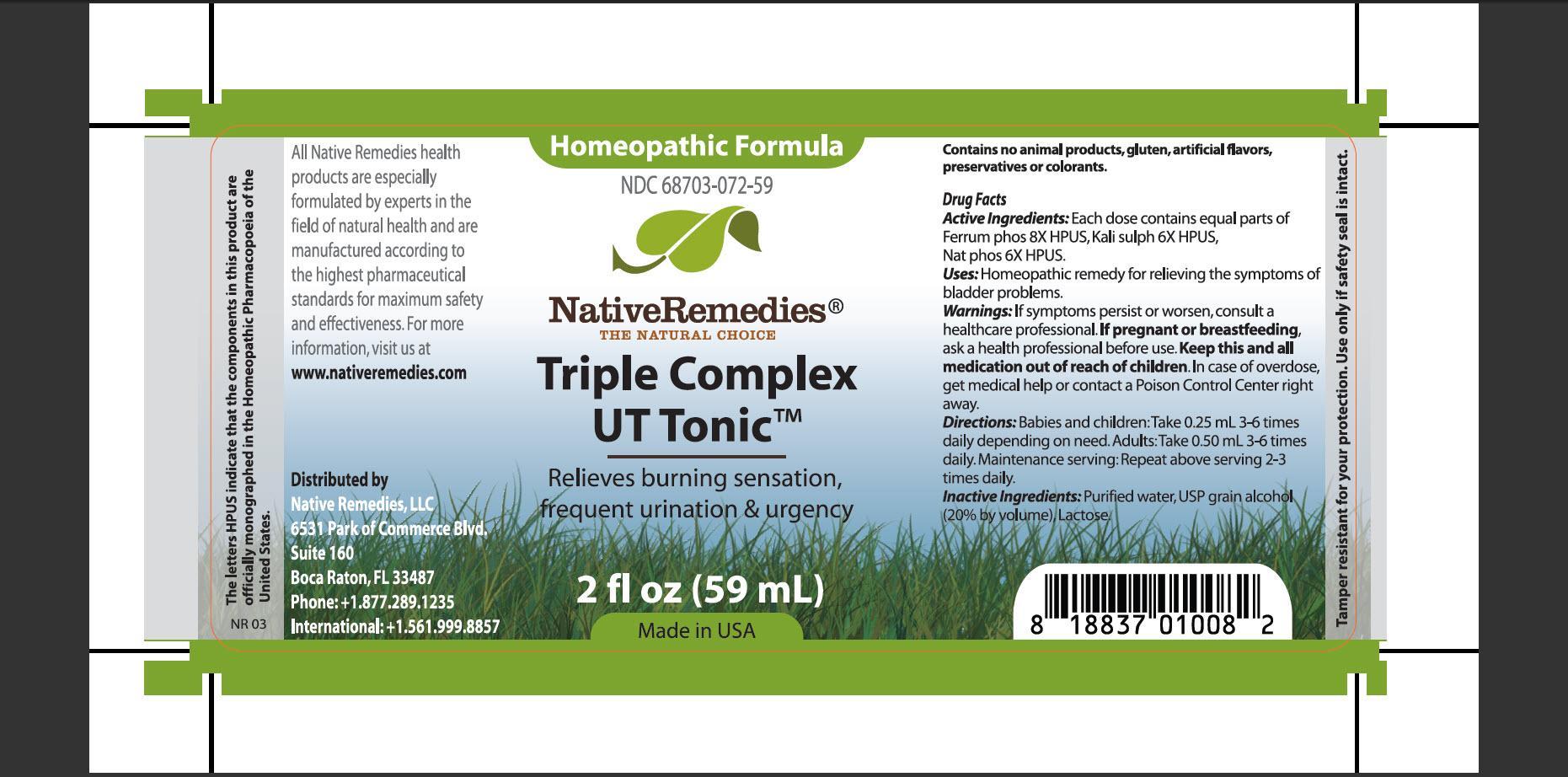 DRUG LABEL: Triple Complex UT Tonic
NDC: 68703-072 | Form: TINCTURE
Manufacturer: Native Remedies, LLC
Category: homeopathic | Type: HUMAN OTC DRUG LABEL
Date: 20130424

ACTIVE INGREDIENTS: FERROSOFERRIC PHOSPHATE 8 [hp_X]/1 mL; POTASSIUM SULFATE 6 [hp_X]/1 mL; SODIUM PHOSPHATE, DIBASIC, HEPTAHYDRATE 6 [hp_X]/1 mL
INACTIVE INGREDIENTS: WATER; ALCOHOL; LACTOSE

Triple Complex UT Tonic

PURPOSE

Relieves burning sensation, frequent urination and urgency

ACTIVE INGREDIENT

Active Ingredients: Each dose contains equal parts of Ferrum phos 8X HPUS, Kali sulph 6X HPUS, Nat phos 6X HPUS

INDICATIONS AND USAGE

Uses: Homeopathic remedy for relieving the symptoms of bladder problems

WARNINGS

Warnings: If symptoms persist or worsen, consult a health professional

PREGNANCY OR BREAST FEEDING

If pregnant or breastfeeding, ask a health professional before use

KEEP OUT OF REACH OF CHILDREN

Keep this and all medication out of reach of children

OVERDOSAGE

In case of overdose, get medical help or contact a Poison Control Center right away

DOSAGE AND ADMINISTRATION

Directions: Babies and children: Take 0.25 mL 3-6 times daily depending on need. Adults: Take 0.50 ml 3-6 times daily. Maintenance serving: Repeat above serving 2-3 times daily

INACTIVE INGREDIENT

Inactive Ingredients: Purified water, USP grain alcohol (20% by volume), Lactose

PATIENT COUNSELING INFORMATION

The letters HPUS indicate that the component in this product are officially monographed in the Homeopathic Pharmacopoeia of the United States

All Native Remedies health product are especially formulated by experts in the field of natural health and are manufactured according to the highest pharmaceutical standards for maximum safety and effectiveness. For more information, visit us at www.nativeremedies.com

Distributed by
Native Remedies, LLC
6531 Park of Commerce Blvd.
Suite 160
Boca Raton, Fl 33487
Phone: +1.877.289.1235
International:+1.561.999.8857

Contains no animal products, gluten, artificial flavors, preservatives or colorants

STORAGE AND HANDLING

Tamper resistant for your protection. Use only if safety seal is intact